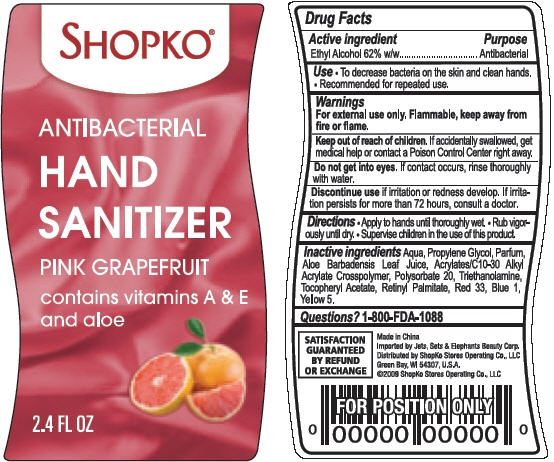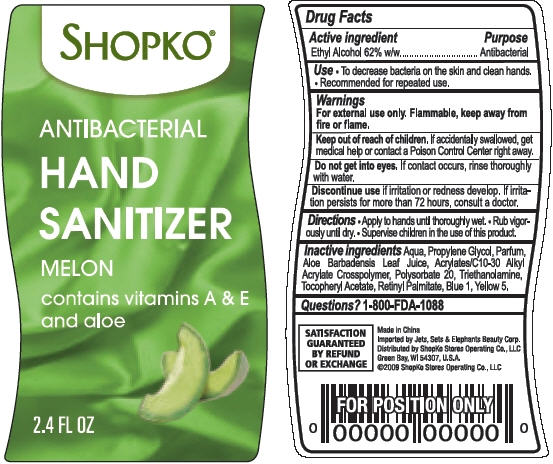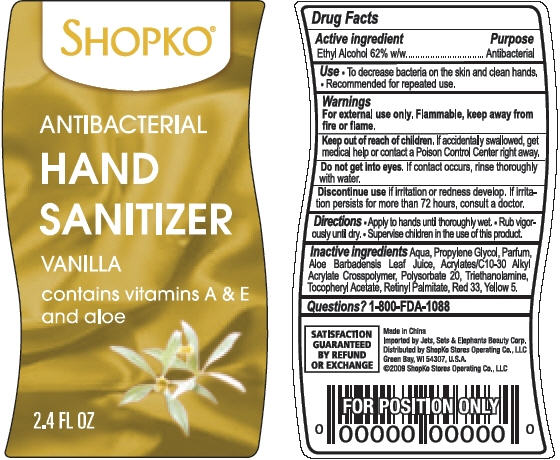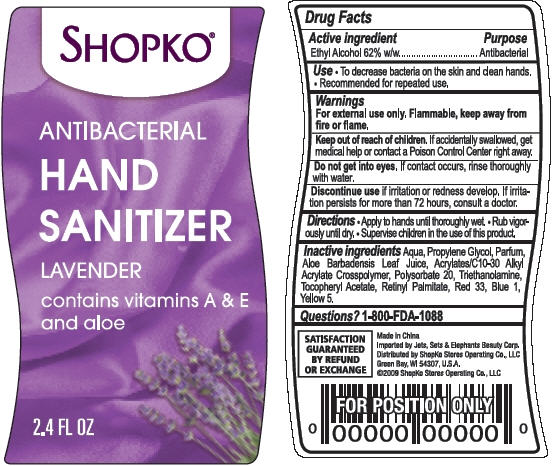 DRUG LABEL: Shopko Antibacterial Hand Sanitizer
NDC: 50988-150 | Form: GEL
Manufacturer: Jets, Sets, & Elephants Beauty Corp.
Category: otc | Type: HUMAN OTC DRUG LABEL
Date: 20100514

ACTIVE INGREDIENTS: ALCOHOL 0.62 mL/1 mL

SHOPKO® Antibacterial Hand Sanitizer - Pink Grapefruit, Melon, Vanilla and Lavender

ACTIVE INGREDIENT

Ethyl Alcohol 62% w/w

PURPOSE

Antibacterial

USE

- To decrease bacteria on the skin and clean hands.
- Recommended for repeated use.

WARNINGS

For external use only. Flammable, keep away from fire or flame.

Keep out of reach of children.

If accidentally swallowed, get medical help or contact a Poison Control Center right away.

Do not get into eyes.

If contact occurs, rinse thoroughly with water.

Discontinue use

if irritation or redness develop. If irritation persists for more than 72 hours, consult a doctor.

DIRECTIONS

- Apply to hands until thoroughly wet.
- Rub vigorously until dry.
- Supervise children in the use of this product.

QUESTIONS?

1-800-FDA-1088

Generic Section

SATISFACTION GUARANTEED BY REFUND OR EXCHANGE

Made in China

Imported by Jets, Sets & Elephants Beauty Corp,

Distributed by ShopKo Stores Operating Co., LLC

Green Bay, WI 54307, U.S.A

©2009 ShopKo Stores Operating Co., LLC

PACKAGE/LABEL PRINCIPAL DISPLAY PANEL

SHOPKO®

ANTIBACTERIAL

HAND SANITIZER

PINK GRAPEFRUIT

contains vitamins A & E

and aloe

2.4 FL OZ

PACKAGE/LABEL PRINCIPAL DISPLAY PANEL

SHOPKO®

ANTIBACTERIAL

HAND SANITIZER

MELON

contains vitamins A & E

and aloe

2.4 FL OZ

PACKAGE/LABEL PRINCIPAL DISPLAY PANEL

SHOPKO®

ANTIBACTERIAL

HAND SANITIZER

VANILLA

contains vitamins A & E

and aloe

2.4 FL OZ

PACKAGE/LABEL PRINCIPAL DISPLAY PANEL

SHOPKO®

ANTIBACTERIAL

HAND SANITIZER

LAVENDER

contains vitamins A & E

and aloe

2.4 FL OZ